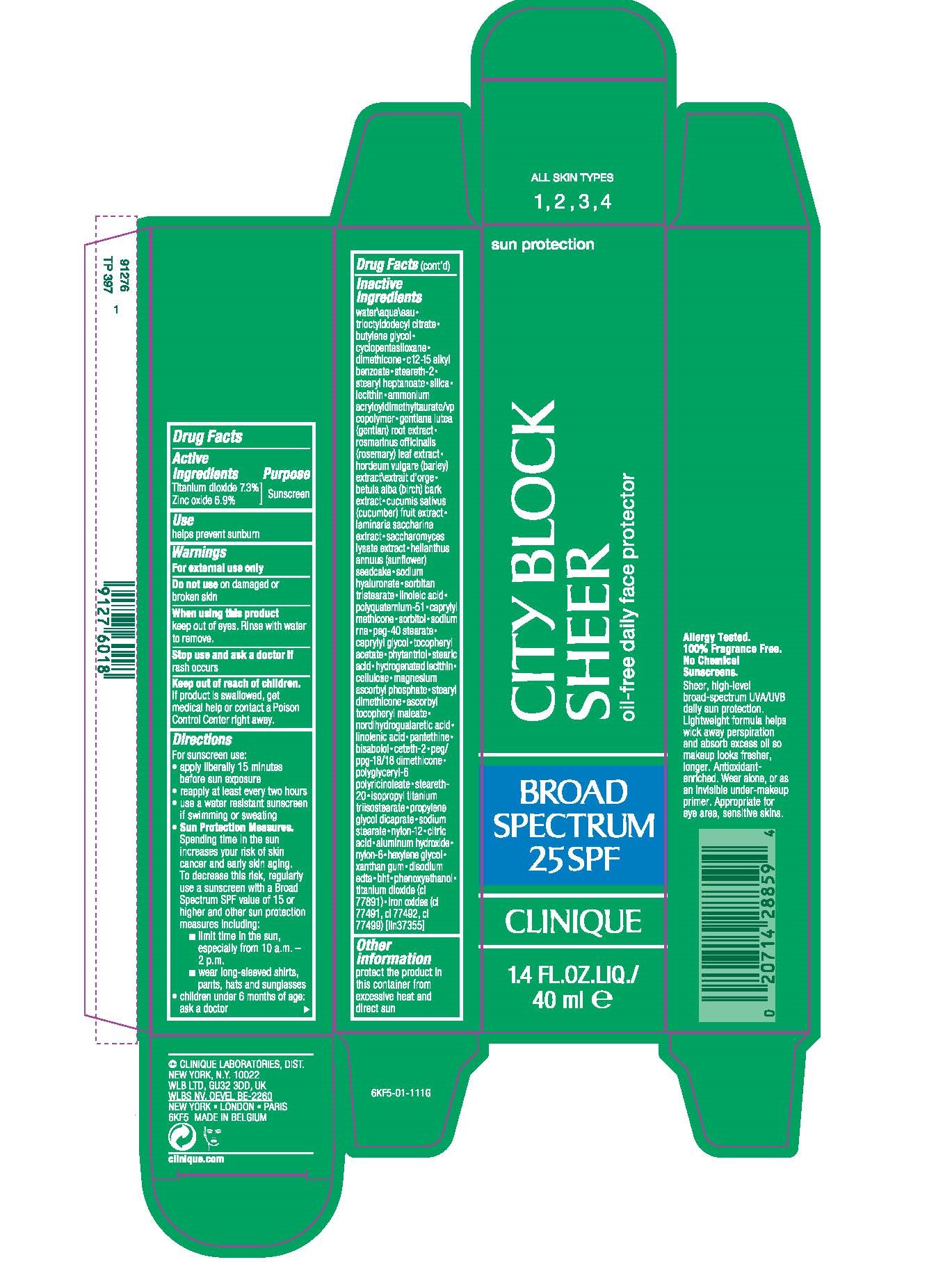 DRUG LABEL: CITY BLOCK SHEER Oil FREE DAILY FACE PROTECTOR BROAD SPECTRUM SPF 25
NDC: 49527-023 | Form: CREAM
Manufacturer: CLINIQUE LABORATORIES LLC
Category: otc | Type: HUMAN OTC DRUG LABEL
Date: 20241225

ACTIVE INGREDIENTS: TITANIUM DIOXIDE 73 mg/1 mL; ZINC OXIDE 69 mg/1 mL
INACTIVE INGREDIENTS: WATER; TRIOCTYLDODECYL CITRATE; BUTYLENE GLYCOL; CYCLOMETHICONE 5; DIMETHICONE; ALKYL (C12-15) BENZOATE; STEARETH-2; STEARYL HEPTANOATE; SILICON DIOXIDE; AMMONIUM ACRYLOYLDIMETHYLTAURATE/VP COPOLYMER; GENTIANA LUTEA ROOT; ROSEMARY; BARLEY; CUCUMBER; SACCHARINA LATISSIMA; SACCHAROMYCES LYSATE; HELIANTHUS ANNUUS SEEDCAKE; HYALURONATE SODIUM; SORBITAN TRISTEARATE; LINOLEIC ACID; CAPRYLYL TRISILOXANE; SORBITOL; PEG-40 STEARATE; CAPRYLYL GLYCOL; .ALPHA.-TOCOPHEROL ACETATE; PHYTANTRIOL; STEARIC ACID; HYDROGENATED SOYBEAN LECITHIN; POWDERED CELLULOSE; MAGNESIUM ASCORBYL PHOSPHATE; STEARYL DIMETHICONE (400 MPA.S AT 50C); ASCORBYL TOCOPHERYL MALEATE; LINOLENIC ACID; PANTETHINE; LEVOMENOL; CETETH-2; PEG/PPG-18/18 DIMETHICONE; STEARETH-20; ISOPROPYL TITANIUM TRIISOSTEARATE; PROPYLENE GLYCOL DICAPRATE; SODIUM STEARATE; NYLON-12; CITRIC ACID MONOHYDRATE; ALUMINUM HYDROXIDE; HEXYLENE GLYCOL; XANTHAN GUM; EDETATE DISODIUM ANHYDROUS; BUTYLATED HYDROXYTOLUENE; PHENOXYETHANOL; FERRIC OXIDE RED; FERRIC OXIDE YELLOW; FERROSOFERRIC OXIDE

CITY BLOCK SHEER OIL FREE DAILY FACE PROTECTOR BROAD SPECTRUM SPF 25

Drug Facts

Active ingredients

Titanium dioxide 7.3%
Zinc oxide 6.9%

Purpose

Sunscreen

Use

helps prevent sunburn

Warnings

For external use only

Do not use on damaged or broken skin

When using this product keep out of eyes. Rinse with water to remove.

Stop use and ask a doctor if rash occurs

Keep out of reach of children. If product is swallowed, get medical help or contact a Poison Control Center right away.

Directions

For sunscreen use:

- apply liberally 15 minutes before sun exposure
- reapply at least every two hours
- use a water resistant sunscreen if swimming or sweating
- Sun Protection Measures. Spending time in the sun increases your risk of skin cancer and early skin aging. To decrease this risk, regularly use a sunscreen with a Broad Spectrum SPF value of 15 or higher and other sun protection measures including:
  - limit time in the sun, especially from 10 a.m. – 2 p.m.
  - wear long-sleeved shirts, pants, hats and sunglasses
- children under 6 months of age: ask a doctor

Inactive ingredients

water\aqua\eau • trioctyldodecyl citrate • butylene glycol • cyclopentasiloxane • dimethicone • c12-15 alkyl benzoate • steareth-2 • stearyl heptanoate • silica • lecithin • ammonium acryloyldimethyltaurate/vp copolymer • gentiana lutea (gentian) root extract • rosmarinus officinalis (rosemary) leaf extract • hordeum vulgare (barley) extract\extrait d'orge • betula alba (birch) bark extract • cucumis sativus (cucumber) fruit extract • laminaria saccharina extract • saccharomyces lysate extract • helianthus annuus (sunflower) seedcake • sodium hyaluronate • sorbitan tristearate • linoleic acid • polyquaternium-51 • caprylyl methicone • sorbitol • sodium rna • peg-40 stearate • caprylyl glycol • tocopheryl acetate • phytantriol • stearic acid • hydrogenated lecithin • cellulose • magnesium ascorbyl phosphate • stearyl dimethicone • ascorbyl tocopheryl maleate • nordihydroguaiaretic acid • linolenic acid • pantethine • bisabolol • ceteth-2 • peg/ppg-18/18 dimethicone • polyglyceryl-6 polyricinoleate • steareth-20 • isopropyl titanium triisostearate • propylene glycol dicaprate • sodium stearate • nylon-12 • citric acid • aluminum hydroxide • nylon-6 • hexylene glycol • xanthan gum • disodium edta • bht • phenoxyethanol • titanium dioxide (ci 77891) • iron oxides (ci 77491, ci 77492, ci 77499) [iln37355]

Other information

protect the product in this container from excessive heat and direct sun

PRINCIPAL DISPLAY PANEL - 40 ml Tube Carton

sun protection

CITY BLOCK
SHEER
oil-free daily face protector

BROAD
SPECTRUM
25 SPF

CLINIQUE

1.4 FL.OZ.LIQ./
40 ml e